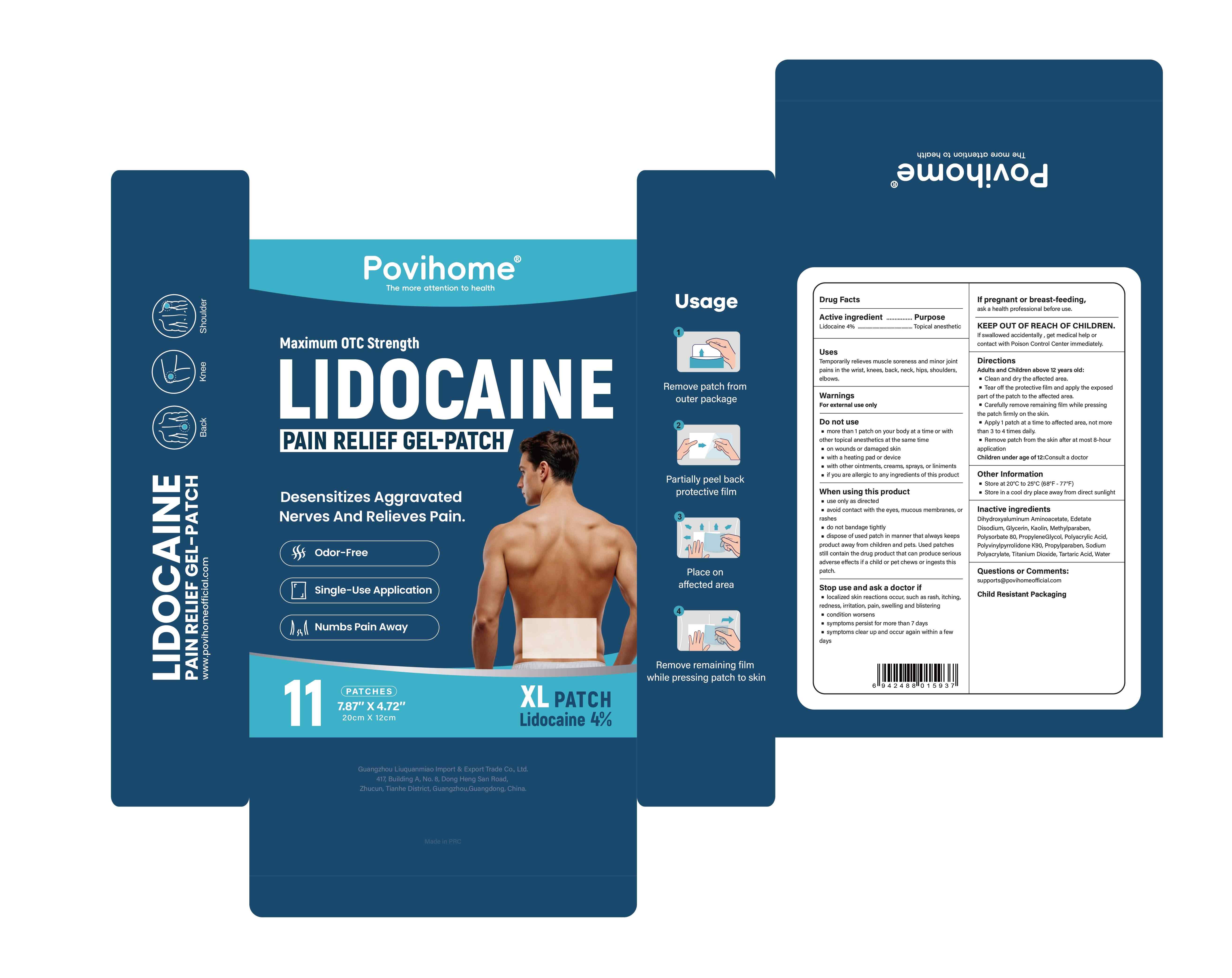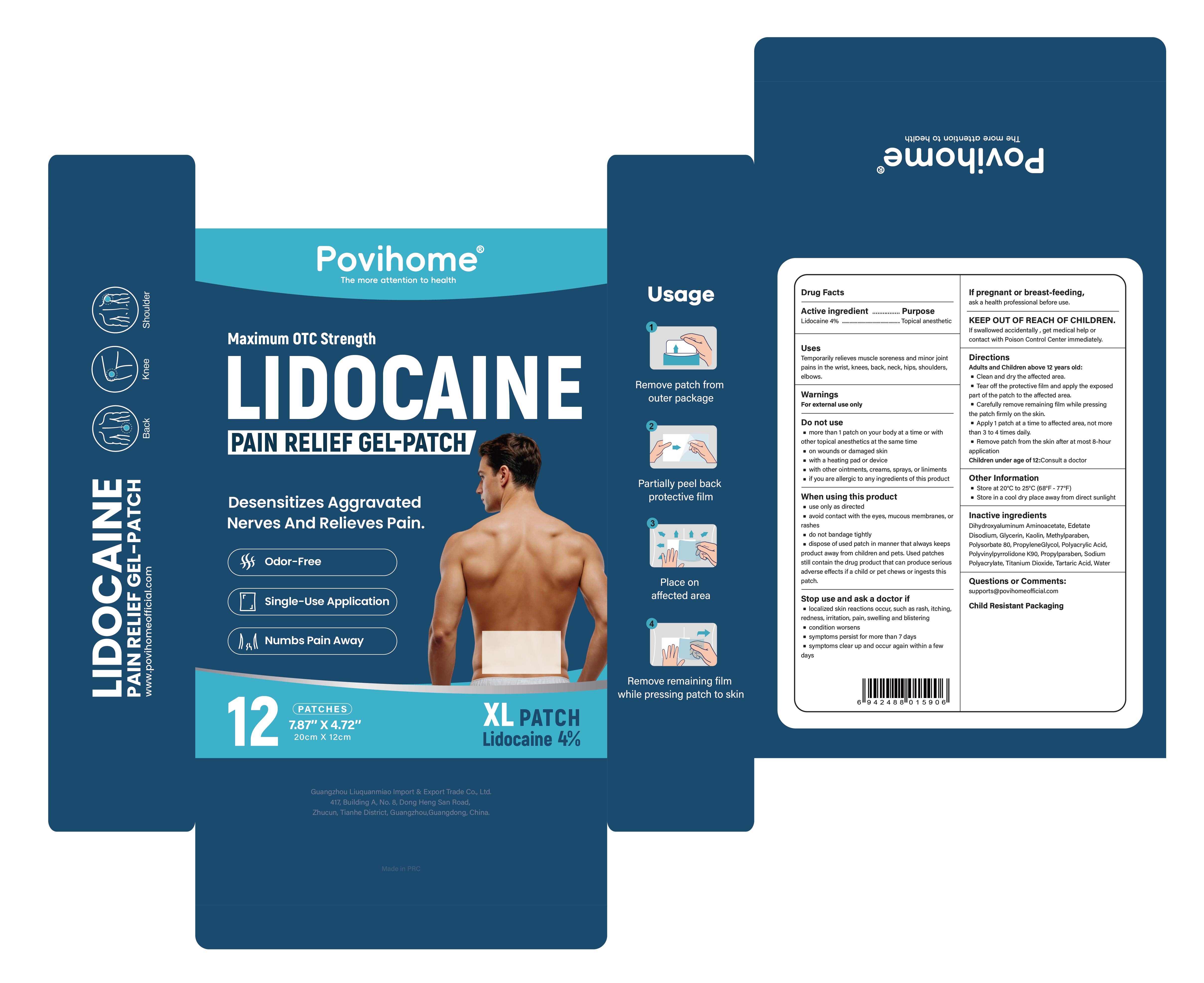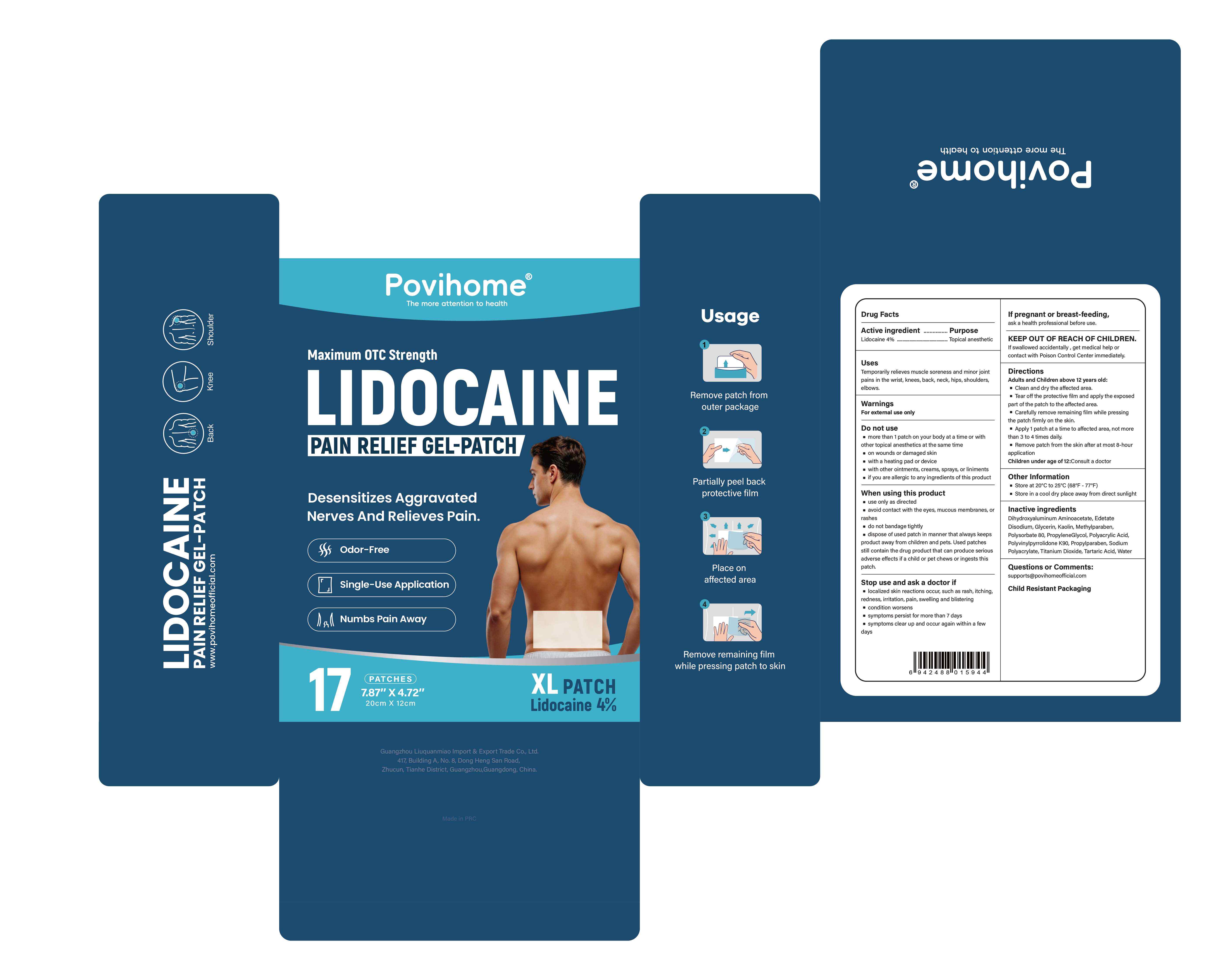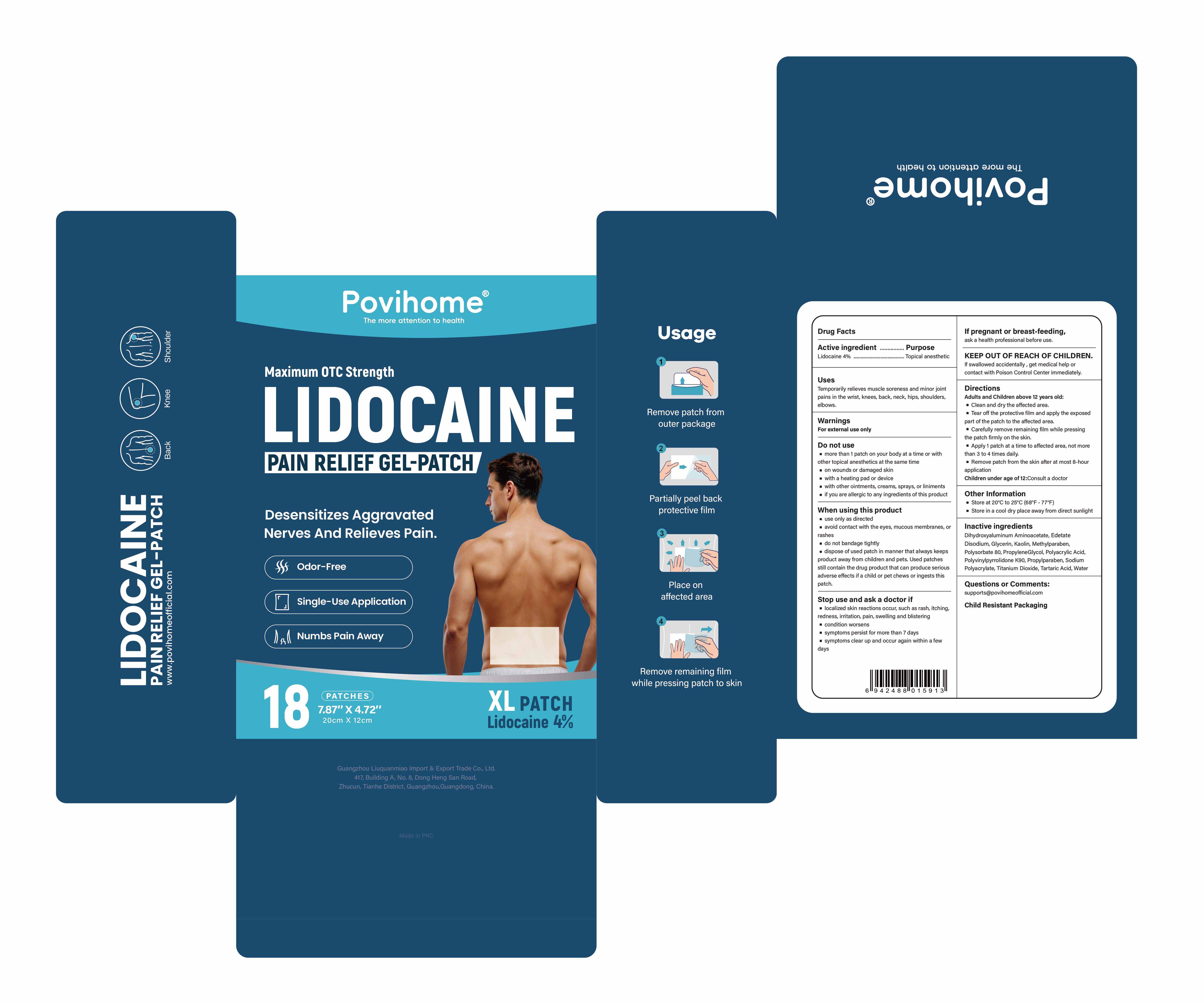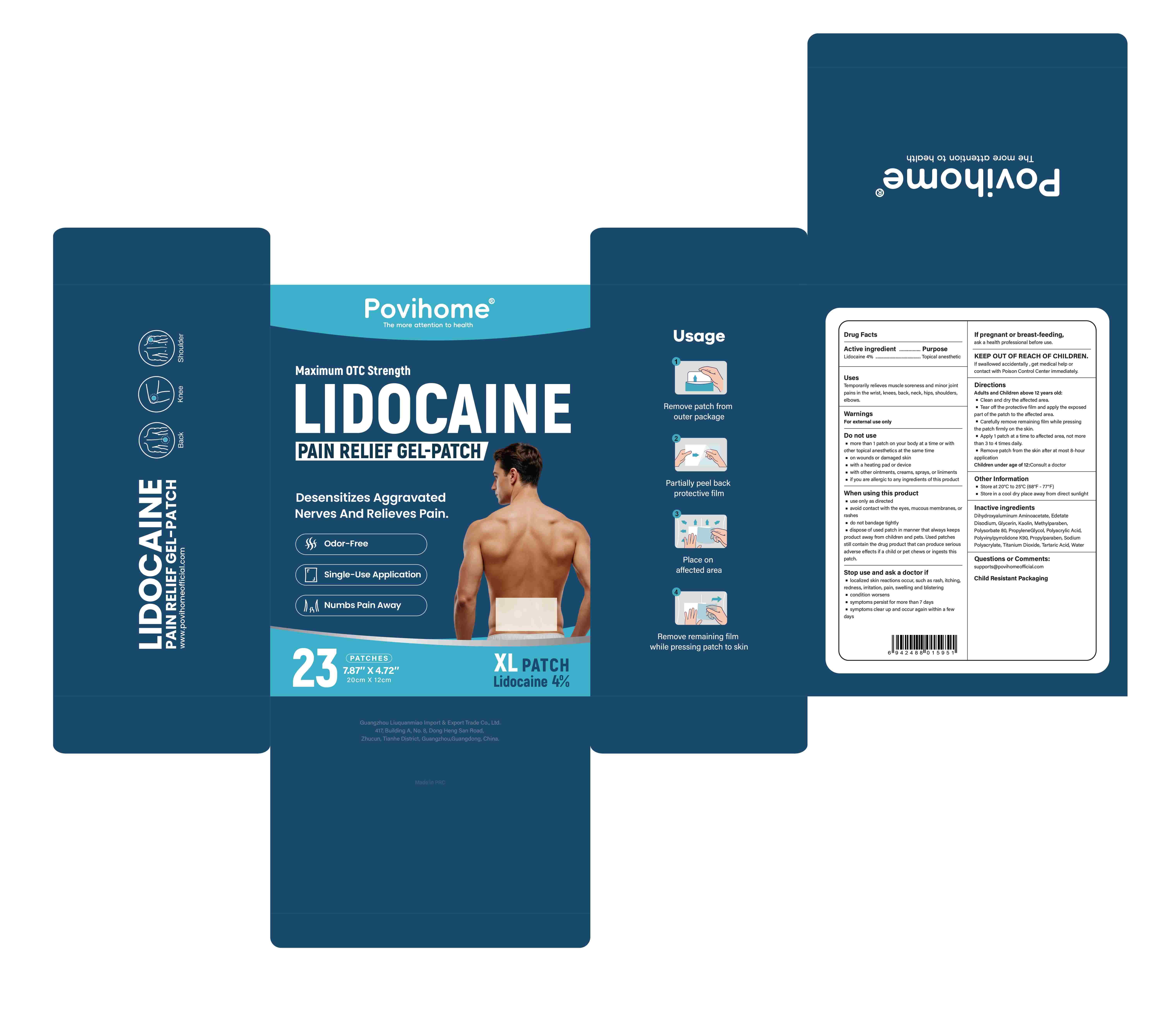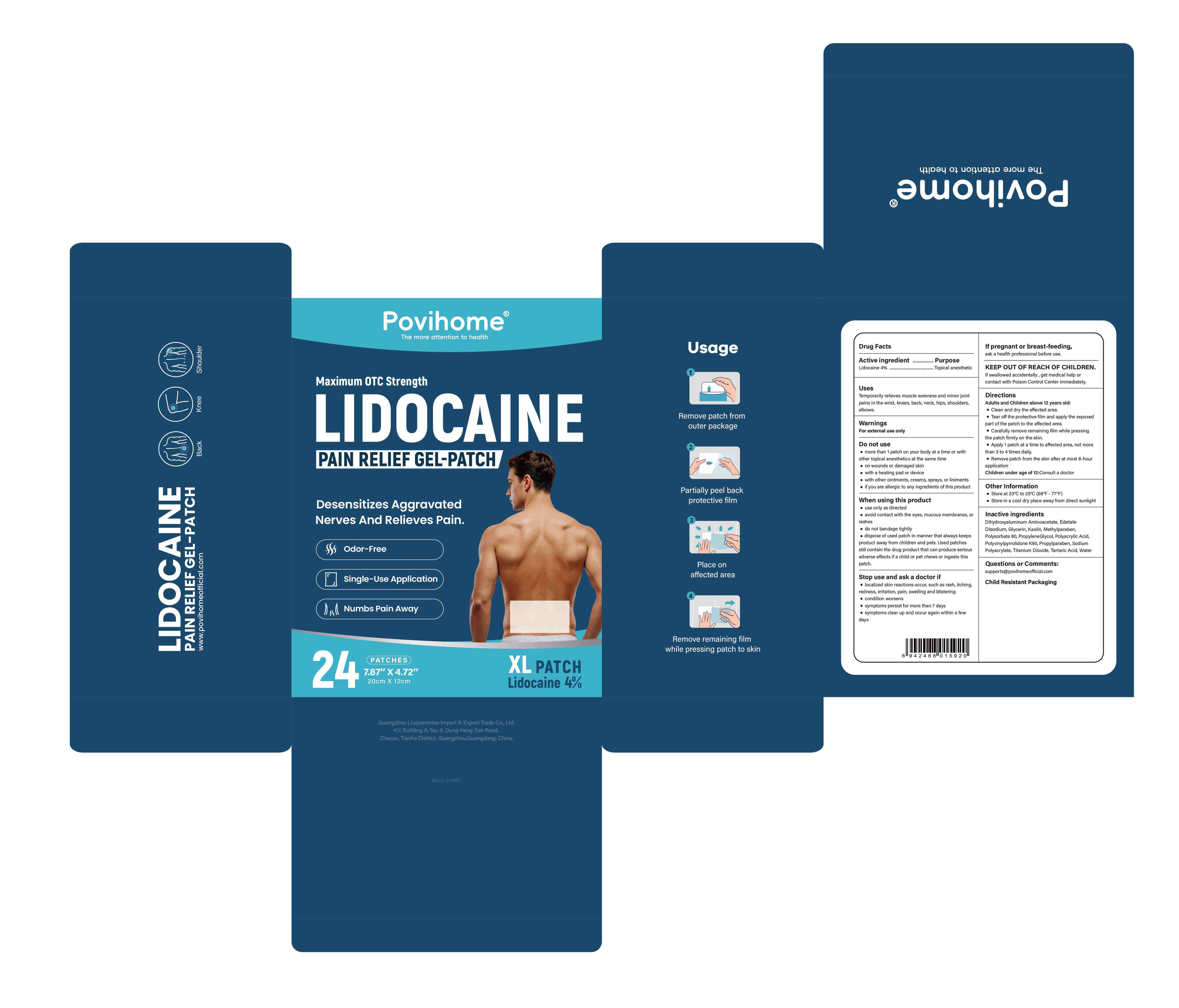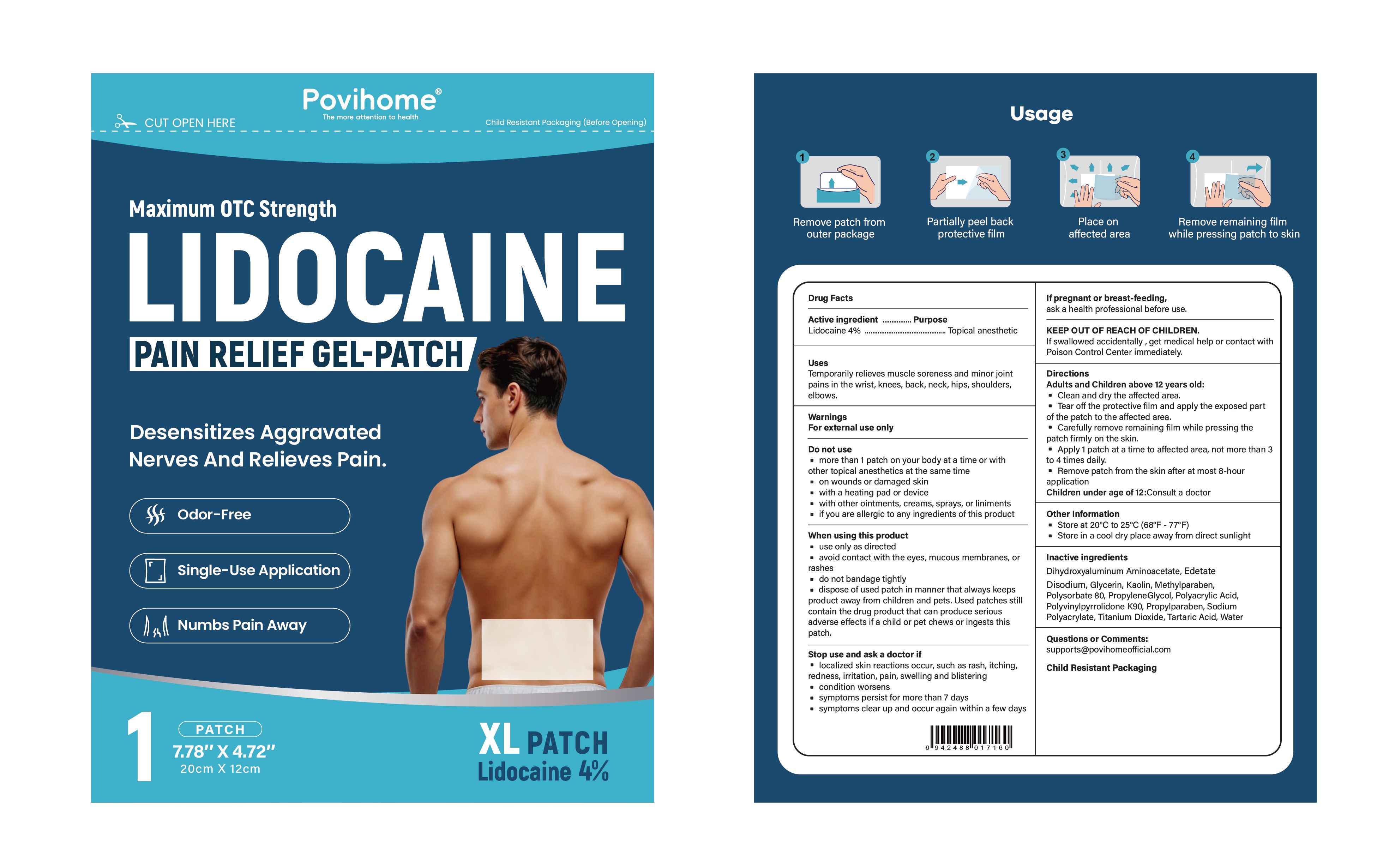 DRUG LABEL: Lidocaine Pain Relief Gel -Patch
NDC: 83602-185 | Form: PATCH
Manufacturer: Guangzhou Liuquanmiao Import & Export Trade Co., Ltd.
Category: otc | Type: HUMAN OTC DRUG LABEL
Date: 20260228

ACTIVE INGREDIENTS: LIDOCAINE 0.04 g/1 g
INACTIVE INGREDIENTS: POLYSORBATE 80; GLYCERIN; POVIDONE K90; METHYLPARABEN; PROPYLPARABEN; EDETATE DISODIUM; KAOLIN; TARTARIC ACID; WATER; PROPYLENE GLYCOL; POLYACRYLIC ACID (250000 MW); SODIUM POLYACRYLATE (2500000 MW); TITANIUM DIOXIDE; DIHYDROXYALUMINUM AMINOACETATE ANHYDROUS

83602-185

Active ingredient

Lidocaine 4% ...... Purpose: Topical Anesthetic

Purpose

Topical Anesthetic

Uses

Temporarily relieves muscle soreness and minor joint pains in the wrist, knees, back, neck, hips, shoulders, elbows.

Warnings

For external use only

Do not use

· more than 1 patch on your body at a time or with other topical anesthetics at the same time

· on wounds or damaged skin

· with a heating pad or device

· with other ointments, creams, sprays, or liniments

· if you are allergic to any ingredients of this product

When using this product

· use only as directed

· avoid contact with the eyes, mucous membranes, or rashes

· do not bandage tightly

· dispose of used patch in manner that always keeps product away from children and pets. Used patches still contain the drug product that can produce serious adverse effects if a child or pet chews or ingests this patch.

Ask a doctor if:

· localized skin reactions occur, such as rash, itching, redness, irritation, pain, swelling and blistering

· condition worsens

· symptoms persist for more than 7 days

· symptoms clear up and occur again within a few days

Stop use if:

· localized skin reactions occur, such as rash, itching, redness, irritation, pain, swelling and blistering

· condition worsens

· symptoms persist for more than 7 days

· symptoms clear up and occur again within a few days

Pregnancy or breast feeding

If pregnant or breastfeeding, ask a health professional before use

Keep out of reach of children. If swallowed accidentally , get medical help or contact with Poison Control Center immediately.

Directions

Adults and Children above 12 years old:

· Clean and dry the affected area.

· Tear off the protective film and apply the exposed part of the patch to the affected area.

· Carefully remove remaining film while pressing the patch firmly on the skin.

· Apply 1 patch at a time to affected area, not more than 3 to 4 times daily.

· Remove patch from the skin after at most 8-hour application

Children under age of 12:Consult a doctor

Other information

Store at 20°C to 25°C (68°F - 77°F)

Store in a cool dry place away from direct sunlight

Inactive ingredients

Dihydroxyaluminum Aminoacetate, Edetate Disodium, Glycerin, Kaolin, Methylparaben, Polysorbate 80, PropyleneGlycol, Polyacrylic Acid, Polyvinylpyrrolidone K90, Propylparaben, Sodium Polyacrylate, Titanium Dioxide, Tartaric Acid, Water

Questions or Comments?

supports@povihomeofficial.com